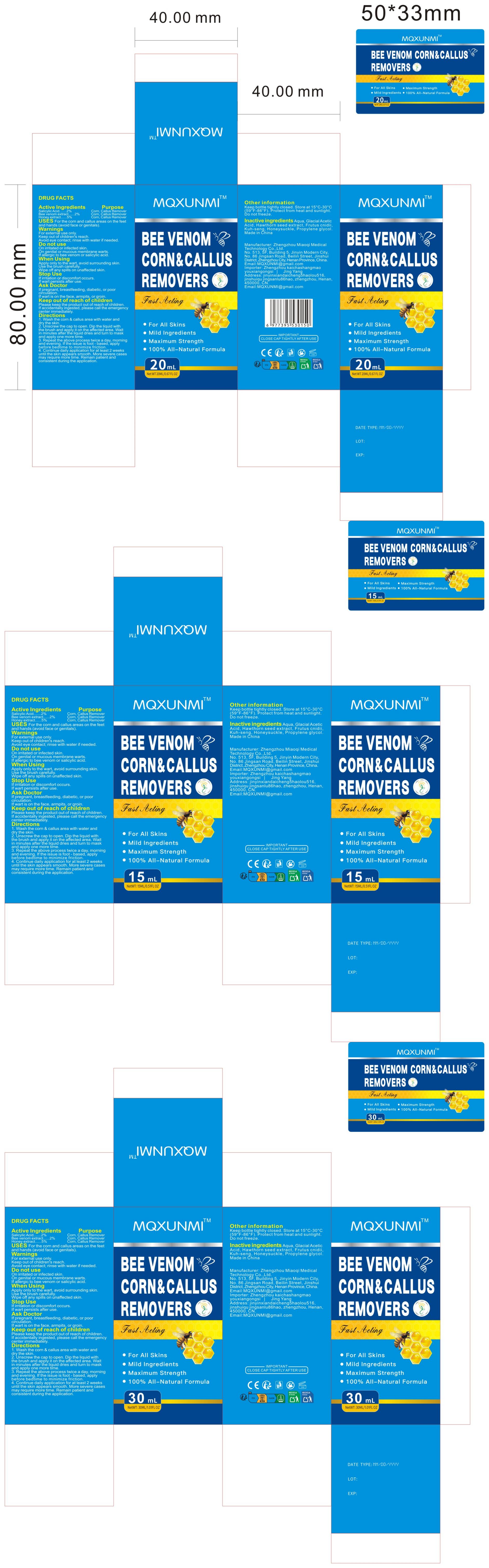 DRUG LABEL: MQXUNMI BEE VENOM CORN CALLUS REMOVERS
NDC: 83781-013 | Form: LIQUID
Manufacturer: Zhengzhou Miaoqi Medical Technology Co., Ltd.
Category: otc | Type: HUMAN OTC DRUG LABEL
Date: 20251020

ACTIVE INGREDIENTS: HONEY 5 g/100 mL; APIS MELLIFERA VENOM 2 g/100 mL; SALICYLIC ACID 2 g/100 mL
INACTIVE INGREDIENTS: KEYHOLE LIMPET HEMOCYANIN 2; CNIDIUM SEED; CRATAEGUS DOUGLASII FRUIT; PROPYLENE GLYCOL; WATER; AQUILEGIA CANADENSIS WHOLE; ACETIC ACID

83781-013

Active Ingredient

Salicylic Acid.......2%
Bee venom extract......2%
Honey extract......5%

Purpose

Corn, Callus Remover

Use

For the corn and callus areas on the feet and hands (avoid face or genitals).

Warnings

For external use only.
Keep out of children's reach.
Avoid eye contact; rinse with water if needed.

Do not use

On irritated or infected skin.
On genital or mucous membrane warts.
If allergic to bee venom or salicylic acid.

When Using

Apply only to the wart, avoid surrounding skin.
Use the brush carefully.
Wipe off any spills on unaffected skin.

Stop Use

If irritation or discomfort occurs.
If wart persists after use.

Ask Doctor

If pregnant, breastfeeding, diabetic, or poor circulation.
If wart is on the face, armpits, or groin.

Keep Out Of Reach Of Children

Please keep the product out of reach of children. If accidentally ingested, please call the emergency center immediately.

Directions

1.Wash the corn & callus area with water and dry the skin.
2.Unscrew the cap to open. Dip the liquid with the brush and apply it on the affected area. Wait in minutes after the liquid dries and turn to mask and apply one more time.
3.Repeat the above process twice a day, morning and evening. If the issue is foot - based, apply before bedtime to minimize friction.
4.Continue daily application for at least 2 weeks until the skin appears smooth. More severe cases may require more time. Remain patient and consistent during the application.

Other information

Keep bottle tightly closed. Store at 15°C-30°C (59°F-86°F). Protect from heat and sunlight. Do not freeze.

Inactive ingredients

Aqua, Glacial Acetic Acid, Hawthorn seed extract, Frutus cnidii, Kuh-seng, Honeysuckle, Propylene glycol.

Questions

Email:MQXUNMI@gmail.com